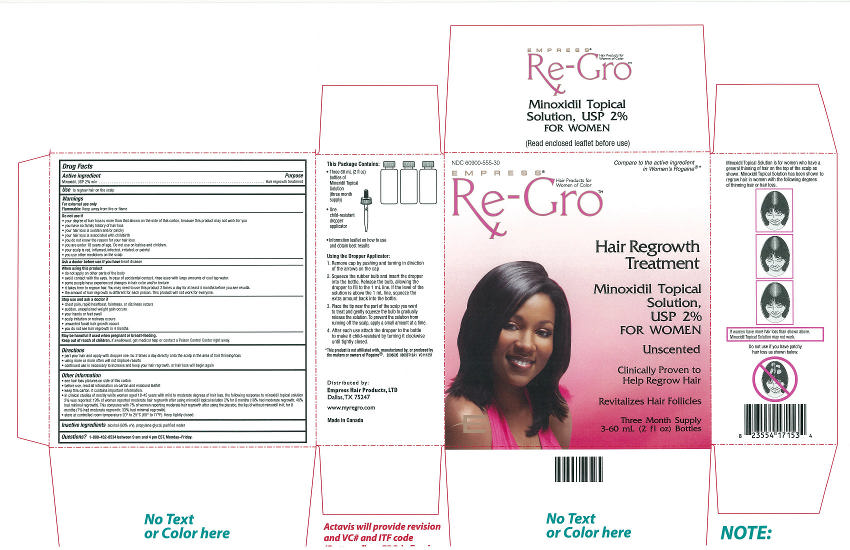 DRUG LABEL: Re-Gro
NDC: 60900-555 | Form: SOLUTION
Manufacturer: Empress Hair Products, Ltd.
Category: otc | Type: HUMAN OTC DRUG LABEL
Date: 20141106

ACTIVE INGREDIENTS: MINOXIDIL 2 g/100 mL
INACTIVE INGREDIENTS: ALCOHOL; PROPYLENE GLYCOL; WATER

Active ingredient

Minoxidil, USP 2% w/v

Purpose

Hair regrowth treatment

INDICATIONS AND USAGE

Use to regrow hair on the scalp

Warnings

For external use only
Flammable: Keep away from fire or flame

Do not use if

- your degree of hair loss is more than that shown on the side of this carton, because this propuct may not work for you
- you have no family history of hair loss
- your hair loss is sudden and/or patchy
- your hair loss is associated with childbirth
- you do not know the reason for your hair loss
- you are under 18 years of age. Do not use on babies and children.
- your scalp is red, inflamed, infected, irritated, or painful
- you use other medicines on the scalp

Ask a doctor before use if you have heart disease

When using this product

- do not apply on other parts of the body
- avoid contact with the eyes. In case of accidental contact, rinse with large amounts of cool tap water.
- some people have experienced changes in hair color and/or texture
- it takes time to regrow hair. You may need to use this product 2 times a day for at least 4 months before you see results.
- the amount of hair regrowth is different for each person. This product will not work for everyone.

Stop use and ask a doctor if

- chest pain, rapid heartbeat, faintness, or dizziness occurs
- sudden, unexplained weight gain occurs
- your hands or feet swell
- scalp irritation or redness occurs
- unwanted facial hair growth occurs
- you do not see hair regrowth in 4 months

KEEP OUT OF REACH OF CHILDREN

May be harmful if used when pregnant or breast-feeding.
Keep out of reach of children. If swallowed, get medical help or contact a Poison Control Center right away.

Directions

- part your hair and apply with dropper one mL 2 times a day directly onto the scalp in the area of hair thinning/loss
- using more or more often will not improve results
- continued use is necessary to increase and keep your hair regrowth, or hair loss will begin again

Other information

- see hair loss pictures on side of this carton
- before use, read all information on carton and enclosed leaflet
- keep this carton. It contains important information.
- in clinical studies of mostly white women aged 18-45 years with mild to moderate degrees of hair loss, the following response to minoxidil topical solution 2% was reported: 19% of women reported moderate hair regrowth after using minoxidil topical solution 2% for 8 months (19% had moderate regrowth; 40% had minimal regrowth). This compares with 7% of women reporting moderate hair regrowth after using the placebo, the liquid without minoxidil in it, for 8 months (7% had moderate regrowth; 33% had minimal regrowth).
- store at controlled room temperature 20° to 25°C (68° to 77°F). Keep tightly closed.

INACTIVE INGREDIENT

Inactive ingredients alcohol (60% v/v), propylene glycol, purified water

QUESTIONS

Questions? 1-800-432-8534 between 9 am and 4 pm EST, Monday-Friday.

———Package Label.Principal Display Panel———

NDC 60900-555-30

Compare to the active ingredient
in Women's Rogaine®*

EMPRESS®

Re-Gro™ Hair Products for Women of Color

Hair Regrowth
Treatment

Minoxidil Topical
Solution,
USP 2%
FOR WOMEN

Unscented

Clinically Proven to
Help Regrow Hair

Revitalized Hair Follicles

Three Month Supply
3-60 mL (2 fl oz) Bottles